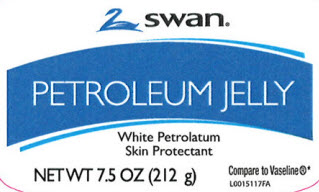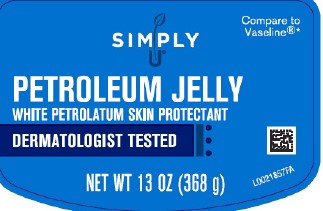 DRUG LABEL: Petroleum Skin Protectant
NDC: 11344-069 | Form: JELLY
Manufacturer: Consumer Product Partners, LLC
Category: otc | Type: HUMAN OTC DRUG LABEL
Date: 20250203

ACTIVE INGREDIENTS: PETROLATUM 1 g/1 g

Swan_Simply U 069.001/069AA
Petroleum Jelly

Active ingredient

White petrolatum USP (100%)

Purpose

Skin protectant

Uses

- temporarily protects minor:
- cuts
- scrapes
- burns
- temporarily protects and helps relieve chapped or cracked skin and lips
- helps protect from the drying effects of wind and cold weather

Warnings

For external use only

Do not use on

- deep or puncture wounds
- animal bites
- serious burns

When using this product

- do not get into eyes

Stop use and ask a doctor if

- condition worsens
- symptoms last more than 7 days or clear up and occur again within a few days

Keep out of reach of children.

If swallowed, get medical help or contact a Poison Control Center right away.

Directions

apply as needed

Inactive Ingredients

None

Adverse reaction

Distributed by:

Consumer Product Partners, LLC

St. Louis, MO 63114

1-888-593-0593

Disclaimer

*This product is not manufactured or distributed by Unilever, distributor of Vaseline ®Original Healing Jelly ®100% White Petroleum Skin Protectant.

Principal display panel

Swan

PETROLEUM JELLY

SKIN PROTECTANT

PETROLEUM JELLY

NET WT 7.5 OZ (212 g)

Compare to Vaseline®*

Principal display panel

Compare to Vaseline®*

SIMPLY U ®

PETROLEUM JELLY

WHITE PETROLEUM SKIN PROTECTANT

DERMATOLOGIST TESTED

NET WT 13 OZ (368 g)